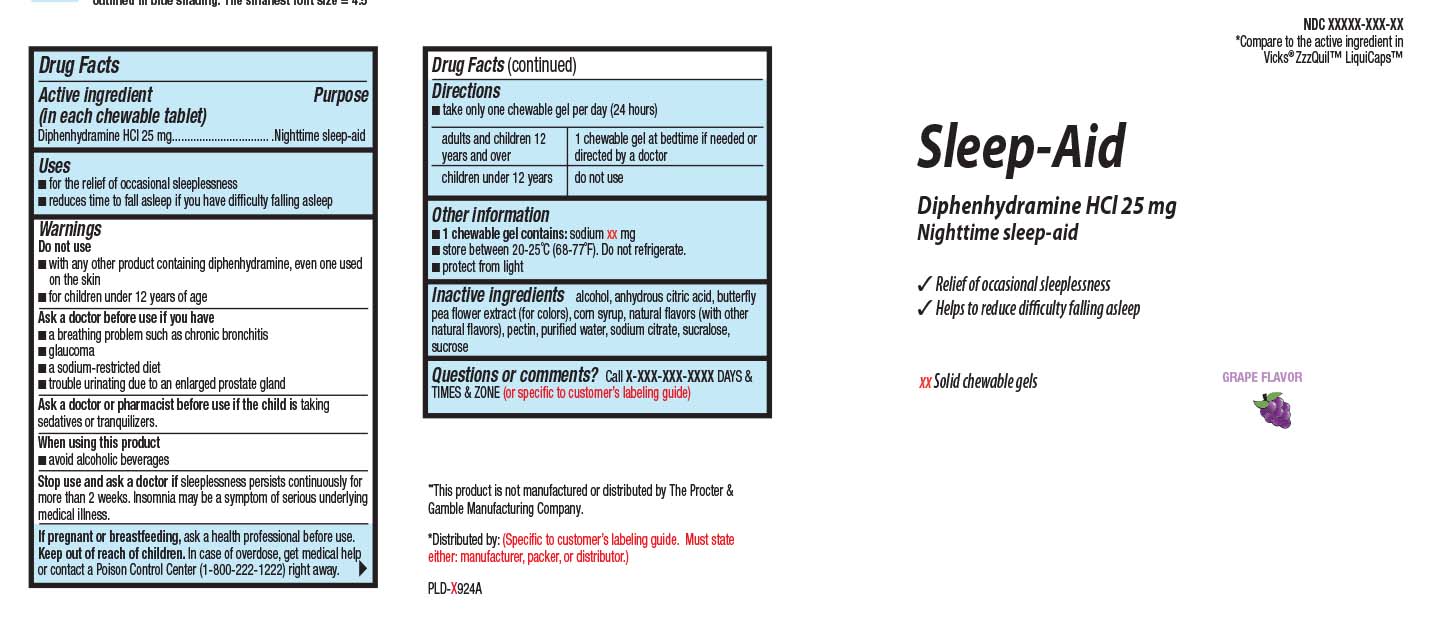 DRUG LABEL: Sleep Aid
NDC: 0363-9236 | Form: CHEWABLE GEL
Manufacturer: Walgreens
Category: otc | Type: HUMAN OTC DRUG LABEL
Date: 20260115

ACTIVE INGREDIENTS: DIPHENHYDRAMINE HYDROCHLORIDE 25 mg/1 1
INACTIVE INGREDIENTS: ALCOHOL; ANHYDROUS CITRIC ACID; CORN SYRUP; PECTIN; WATER; SUCRALOSE; SUCROSE; SODIUM CITRATE

Drug Facts

Active ingredient (in each caplet)

Diphenhydramine HCl 25 mg

Purpose

Nighttime sleep-aid

Uses

- for the relief of occasional sleeplessness
- reduce time to fall asleep if you have difficulty falling asleep

Warnings

Do not use

- with any other products containing diphenhydramine, even one used on skin
- in children under 12 years of age

Ask a doctor before use if you have

- a breathing problem such as emphysema or chronic bronchitis
- glaucoma
- a sodium-restricted diet
- trouble urinating due to an enlarged prostate gland

Ask a doctor or pharmacist before use if you are

taking sedatives or tranquilizers.

When using this product

- avoid alcoholic beverages

Stop use and ask a doctor if

- sleeplessness persists for more than 2 weeks. Insomnia may be a symptom of a serious underlying medical illness.

If pregnant or breast-feeding,

ask a health professional before use.

Keep out of reach of children.

In case of overdose, get medical help or contact a Poison Control Center (1-800-222-1222) right away.

Directions

- take only one chewable gel per day (24 hours)

adults and children 12 years and over | 1 chewable gel at bedtime if needed or directed by a doctor
children under 12 years | do not use

Other information

- 1 chewable gel contains: sodium
- store between 20-25ºC (68-77ºF). Do not refrigerate
- protect from light

Questions or comments?

Call 1-877-753-3935 Monday-Friday 9AM-5PM EST

Inactive ingredient

Alcohol, anhydrous citric acid, butterfly pea flower extract (for color), corn syrup, natural flavors (with other natural flavors) pectin, purified water, sodium citrate, sucralose, sucrose

Principal Display Panel

Compare to the active ingredient in Vicks® ZzzQuil™

Nighttime SLEEP-AID

DIPHENHYDRAMINE HCl, 25 mg

• For a restful night's sleep

• Safe, non-habit forming

Does not contain pain reliever

This product is not manufactured or distributed by The Procter & GambleCompany. Vicks®, NyQuil™, and LiquiCaps™ are registered trademarks of The Procter & Gamble Company.

KEEP OUTER CARTON FOR COMPLETE WARNINGS AND PRODUCT INFORMATION.

TAMPER EVIDENT: DO NOT USE IF IMPRINTED SAFETY SEAL UNDER CAP IS BROKEN OR MISSING.

Product Label

WALGREENS Sleep_aid Chewable